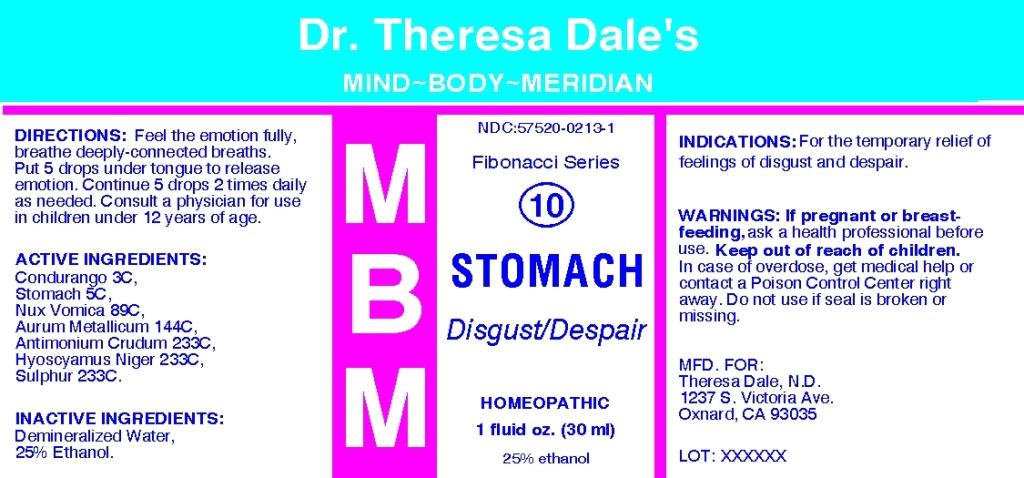 DRUG LABEL: MBM 10 Stomach
NDC: 57520-0213 | Form: LIQUID
Manufacturer: Apotheca Company
Category: homeopathic | Type: HUMAN OTC DRUG LABEL
Date: 20101116

ACTIVE INGREDIENTS: SUS SCROFA STOMACH 5 [hp_C]/1 mL; STRYCHNOS NUX-VOMICA SEED 89 [hp_C]/1 mL; GOLD 144 [hp_C]/1 mL; ANTIMONY TRISULFIDE 233 [hp_C]/1 mL; HYOSCYAMUS NIGER 233 [hp_C]/1 mL; SULFUR 233 [hp_C]/1 mL; MARSDENIA CONDURANGO BARK     3 [hp_C]/1 mL
INACTIVE INGREDIENTS: WATER; ALCOHOL

MBM 10 Stomach

ACTIVE INGREDIENT

ACTIVE INGREDIENTS: Condurango 3C, Stomach 5C, Nux vomica 89C, Aurum metallicum 144C, Antimonium crudum 233C, Hyoscyamus niger 233C, Sulphur 233C.

PURPOSE

INDICATIONS: For the temporary relief of feelings of disgust and despair.

WARNINGS

WARNINGS: If pregnant or breast-feeding, ask a health professional before use. Keep out of reach of children. In case of overdose, get medical help or contact a Poison Control Center right away. Do not use is seal is broken or missing.

DOSAGE AND ADMINISTRATION

DIRECTIONS: Feel the emotion fully, breathe deeply-connected breaths. Put 5 drops under tongue to release emotion. Continue 5 drops 2 times daily as needed. Consult a physician for use in children under 12 years of age.

INACTIVE INGREDIENTS: Demineralized water, 25% Ethanol

KEEP OUT OF REACH OF CHILDREN. In case of overdose, get medical help or contact a Poison Control Center right away.

INDICATIONS AND USAGE

INDICATIONS: For the temporary relief of feelings of disgust and despair.

QUESTIONS

MFD. FOR:

Theresa Dale, N.D.

1237 S Victoria Ave.

Oxnard, CA 93035

PACKAGE LABEL

Dr. Theresa Dale's

MIND BODY MERIDIAN

NDC: 57520 0213 1

Fibonacci Series

10

MBM STOMACH

Disgust/Despair

HOMEOPATHIC

1 fluid oz. (30 ml)